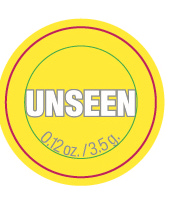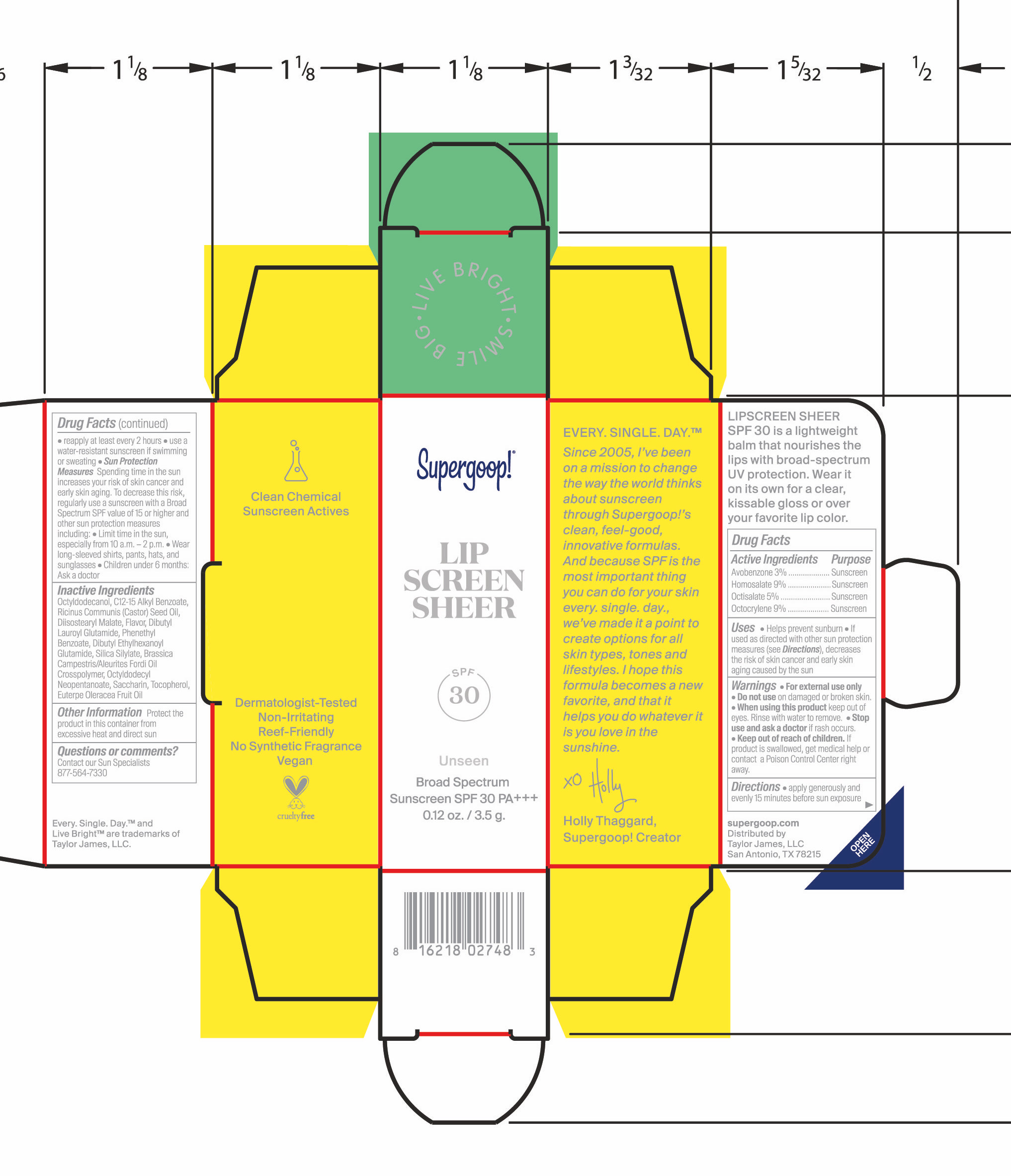 DRUG LABEL: Unseen Sunscreen Lip Protector SPF 30
NDC: 75936-667 | Form: STICK
Manufacturer: Supergoop LLC
Category: otc | Type: HUMAN OTC DRUG LABEL
Date: 20251216

ACTIVE INGREDIENTS: AVOBENZONE 3 mg/100 mL; OCTOCRYLENE 9 mg/100 mL; OCTISALATE 5 mg/100 mL; HOMOSALATE 9 mg/100 mL
INACTIVE INGREDIENTS: SILICA DIMETHYL SILYLATE; OCTYLDODECYL NEOPENTANOATE; SACCHARIN; EUTERPE OLERACEA WHOLE; OCTYLDODECANOL; TOCOPHEROL; DRYOBALANOPS AROMATICA WHOLE; DIBUTYL LAUROYL GLUTAMIDE; DIBUTYL ETHYLHEXANOYL GLUTAMIDE; BRASSICA RAPA VAR. RAPA OIL; PHENETHYL BENZOATE; ALKYL (C12-15) BENZOATE; RICINUS COMMUNIS SEED; DIISOSTEARYL MALATE

Unseen Sunscreen Lip Protector SPF 30

Uses

Help prevent sunburn

If used as directed with other sun protection measures (see Directions), decreases the risk of skin cancer and early skin aging caused by the sun

WARNINGS

For External use only

Do not use on damaged or broken skin

When using this product, keep out of eyes. Rinse with water to remove

Warnings

Do not use on damaged or broken skin.

Warnings

When using this product keep out of eyes. Rinse with water to remove.

Warnings

Stop use and ask a doctor if rash occurs.

Warnings

Keep out of reach of children. If product is swallowed, get medical help of contact a Poison Control Center right away.

Directions

- Apply generously and evenly 15 minutes before sun exposure
- Reapply at least every 2 hours
- use a water-resistant sunscreen if swimming or sweating

Sun Protection Measures Spending time in the sun increases your risk of skin cancer and early skin aging. To decrease this risk, regularly use a sunscreen with a Broad Spectrum SPF value of 15 or higher and other sun protection measures including:

- Limit time in the sun, especially from 10am-2pm
- Wear long-sleeved shirts, pants, hats, and sunglasses
- Children under 6 months: Ask a doctor

Inactive Ingredients

Octoyldodecanol, C12-15 Alkyl Benzoate, Ricinus Communis (Castor) Seed Oil, Diisostearyl Malate, Flavor, Dibutyl Lauroyl Glutamide, Phenethyl Benzoate, Dibutyl Ethylhexanoyl Glutamide, Silica Silylate, Brassica Campestris/Aleurites Fordi Oil Crosspolymer, Octyldodecyl Neopentanoate, Saccharin, Tocopherol, Euterpe Oleracea Fruit Oil

Other Information

Protect the product in this container from excessive heat and direct sun

Questions or comments?

Contact our Sun Specialist

877-564-7330

PURPOSE

Helps prevent sunburn

If used as directed with other sun protection measures (see Directions), decreases the risk of skin cancer and early skin aging caused by the sun

PDP

Lip Screen Sheer SPF 30

Unseen shade